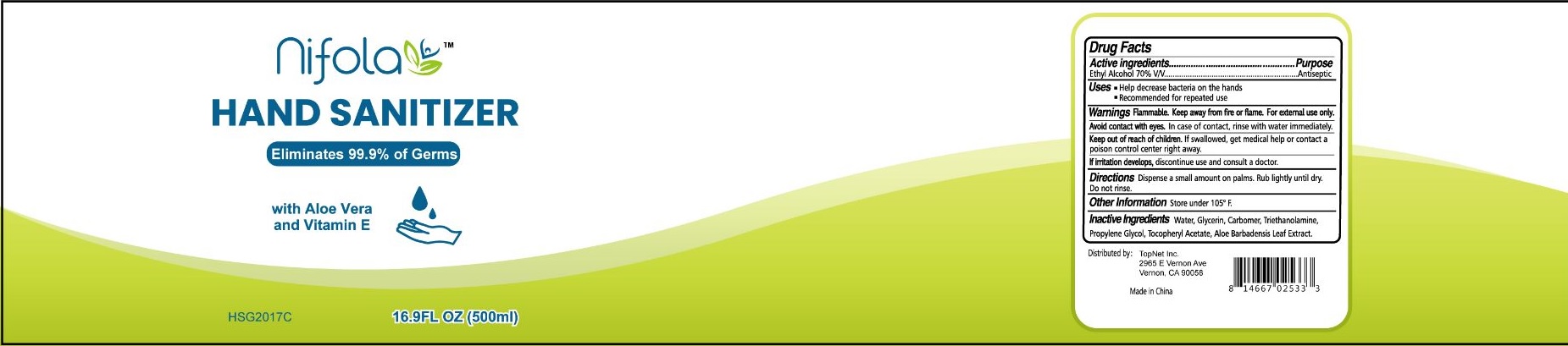 DRUG LABEL: Nifola Hand Sanitizer with Aloe Vera and Vitamin E
NDC: 74149-022 | Form: GEL
Manufacturer: Yiwu Yangjie Daily Chemicals Co.,Ltd.
Category: otc | Type: HUMAN OTC DRUG LABEL
Date: 20200612

ACTIVE INGREDIENTS: alcohol 70 mL/100 mL
INACTIVE INGREDIENTS: WATER; PROPYLENE GLYCOL; ALOE VERA LEAF; GLYCERIN; .ALPHA.-TOCOPHEROL ACETATE; TROLAMINE; ALPHA-TOCOPHEROL

Drug facts

Active ingredient Purpose

Ethyl Alcohol 70% V/V ... Antiseptic

PURPOSE

- help decrease bacteria on the hands.
- recommended for repeated use.

KEEP OUT OF REACH OF CHILDREN

if swallowed, get meical help or contact a poison control center right away.

INDICATIONS AND USAGE

Dispense a small amount on palms. Rub lightly until dry. Do not rinse.

WARNINGS

For external use only.
Flammable. Keep away from fire or flame.

Avoid contact with eyes, in case of contact, rinse with water immediately.

If irritation develops, discontinue use and consult a doctor.

OTHER INFORMATION: store under 105℉.

DOSAGE AND ADMINISTRATION

Dispense a small amount on palms. Rub lightly until dry. Do not rinse.

INACTIVE INGREDIENT

Water, Glycerin, Carbomer, Triethanolamine, Propylene Glycol, Tocopheryl Acetate, Aloe Barbadensis Leaf Extract